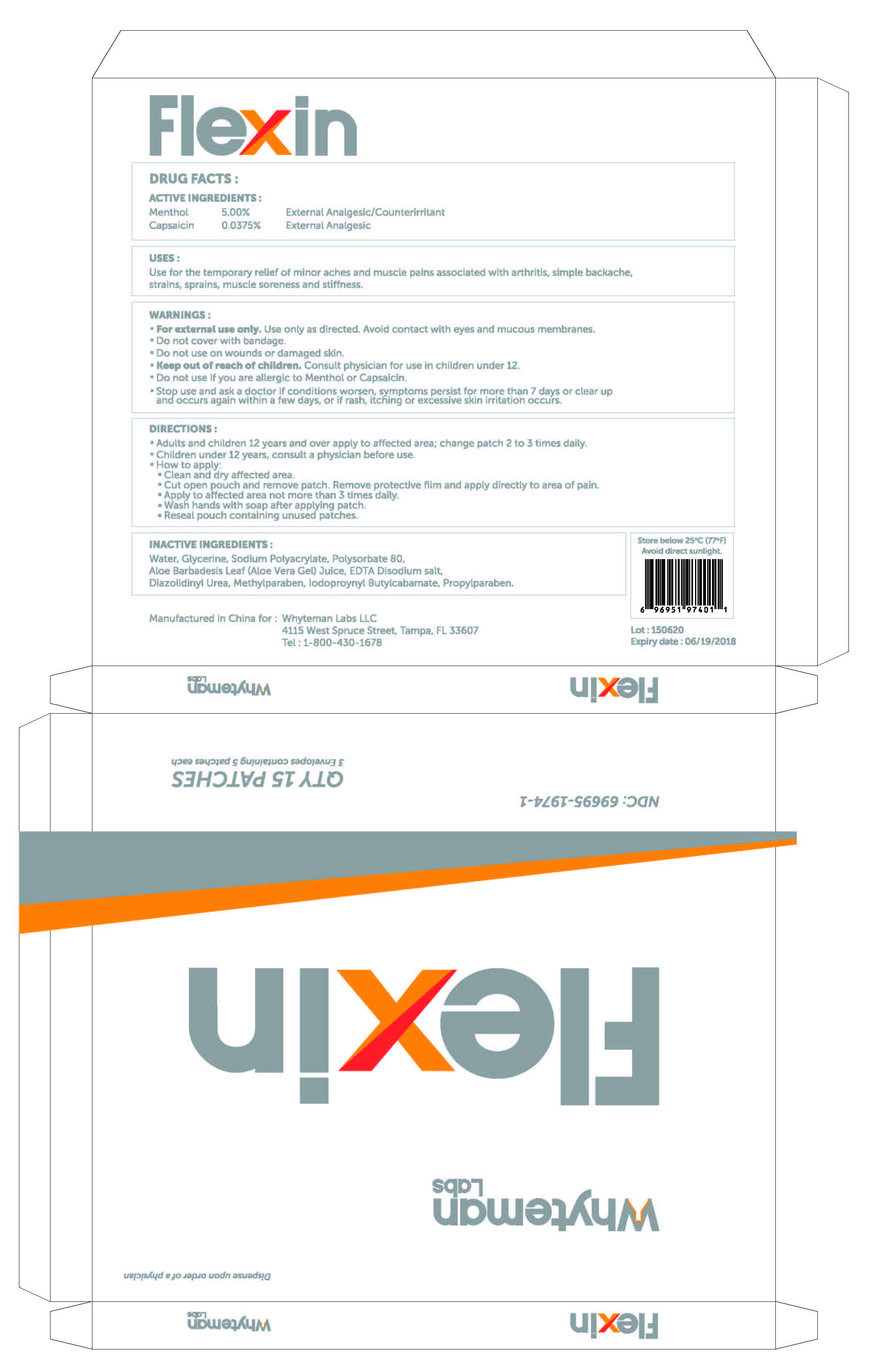 DRUG LABEL: Flexin
NDC: 69695-1974 | Form: PATCH
Manufacturer: Whyteman Labs LLC
Category: otc | Type: HUMAN OTC DRUG LABEL
Date: 20151111

ACTIVE INGREDIENTS: CAPSAICIN 0.000375 1/1 1; MENTHOL 0.05 1/1 1
INACTIVE INGREDIENTS: POLYSORBATE 80; EDETIC ACID; WATER; GLYCERIN; SODIUM POLYACRYLATE (8000 MW); ALOE VERA LEAF; IODOPROPYNYL BUTYLCARBAMATE; PROPYLPARABEN; DIAZOLIDINYL UREA; METHYLPARABEN

ACTIVE INGREDIENT

Menthol 5.00%

PURPOSE

External Analgesic/Counterirritant

ACTIVE INGREDIENT

Capsaicin 0.0375%

PURPOSE

External Analgesic

USES :

Use for the temporary relief of minor aches and muscle pains associated with arthritis, simple backache, strains, sprains, muscle soreness and stiffness.

WARNINGS :

- For external use only. Use only as directed. Avoid contact with eyes and mucous membranes.
- Do not cover with bandage.
- Do not use on wounds or damaged skin.

- Keep out of reach of children. Consult physician for use in children under 12.

- Do not use if you are allergic to Menthol or Capsaicin.

- Stop use and ask a doctor if conditions worsen, symptoms persist for more than 7 days or clear up and occurs again within a few days, or if rash, itching or excessive skin irritation occurs.

DIRECTIONS :

- Adults and children 12 years and over apply to affected area; change patch 2 to 3 times daily.
- Children under 12 years, consult a physician before use.
- How to apply:
- Clean and dry affected area.
- Cut open pouch and remove patch. Remove protective film and apply directly to area of pain.
- Apply to affected area not more than 3 times daily.
- Wash hands with soap after applying patch.
- Reseal pouch containing unused patches.

INACTIVE INGREDIENTS :

Water, Glycerine, Sodium Polyacrylate, Polysorbate 80,

Aloe Barbadesis Leaf (Aloe Vera Gel) Juice, EDTA Disodium salt,

Diazolidinyl Urea, Methylparaben, Iodopropynyl Butylcarbamate, Propylparaben.

STORAGE AND HANDLING

Store below 25°C (77°F)

Avoid direct sunlight.